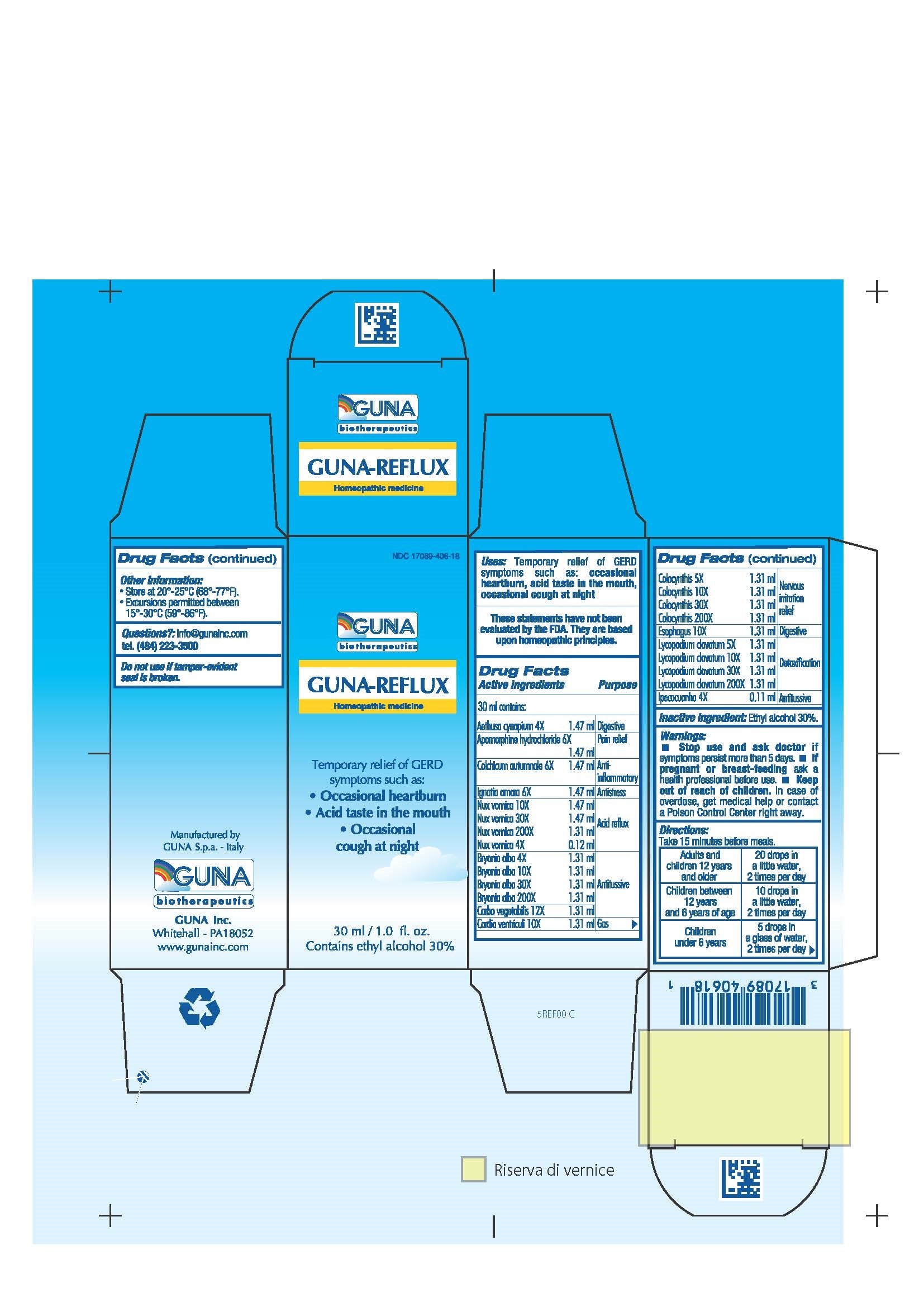 DRUG LABEL: GUNA-REFLUX
NDC: 17089-406 | Form: SOLUTION/ DROPS
Manufacturer: Guna spa
Category: homeopathic | Type: HUMAN OTC DRUG LABEL
Date: 20181221

ACTIVE INGREDIENTS: AETHUSA CYNAPIUM 4 [hp_X]/30 mL; APOMORPHINE HYDROCHLORIDE 6 [hp_X]/30 mL; BRYONIA ALBA ROOT 30 [hp_X]/30 mL; ACTIVATED CHARCOAL 12 [hp_X]/30 mL; SUS SCROFA STOMACH 10 [hp_X]/30 mL; COLCHICUM AUTUMNALE BULB 6 [hp_X]/30 mL; WATERMELON 30 [hp_X]/30 mL; SUS SCROFA ESOPHAGUS 10 [hp_X]/30 mL; STRYCHNOS IGNATII SEED 6 [hp_X]/30 mL; IPECAC 4 [hp_X]/30 mL; LYCOPODIUM CLAVATUM SPORE 5 [hp_X]/30 mL; STRYCHNOS NUX-VOMICA SEED 4 [hp_X]/30 mL
INACTIVE INGREDIENTS: ALCOHOL 9 mL/30 mL

GUNA-REFLUX

ACTIVE INGREDIENTS/PURPOSE

AETHUSA CYNAPIUM 4X DIGESTIVE
APOMORPHINE HYDROCHLORIDE 6X PAIN RELIEF
BRYONIA ALBA 4X, 10X, 30X, 200X ANTITUSSIVE
CARBO VEGETALIS 12X ANTITUSSIVE
CARDIA VENTRICULI 10X GAS
COLCHICUM AUTUMNALE 6X ANTI-INFLAMMATORY
COLOCYNTHIS 5X, 10X, 30X, 200X NERVOUS IRRITATION RELIEF
ESOPHAGUS 10X DIGESTIVE
IGNATIA AMARA 6X ANTISTRESS
IPECACUANHA 4X ANTITUSSIVE
LYCOPODIUM CLAVATUM 5X, 10X, 30X, 200X DETOXIFICATION
NUX VOMICA 4X, 10X, 30X, 200X ACID REFLUX

USES

Temporary relief of GERD symptoms such as:

- Occasional heartburn
- Acir taste in the mouth
- Occasional cough at night

WARNINGS

Stop use and ask doctor if symptoms persist more than 5 days.
If pregnant or breast-feeding ask a health professional before use.
Keep out of reach of children. In case of overdose, get medical help or contact a Poison Control Center right away.
Contains ethyl alcohol 30%

PREGNANCY

If pregnant or breast-feeding ask a doctor before use

DIRECTIONS

Adults and children 12 years and older 10 drops in a little water 3 times per day
Children between 12 years and 6 years of age 7 drops in a little water 3 times per day
Children under 6 years 5 drops in a glass of water 3 times per day

QUESTIONS

Questions?: info@gunainc.com
Tel. (484) 223-3500

INDICATIONS AND USAGE

Take 15 minutes before meals

Inactive ingredient: Ethyl alcohol 30%.